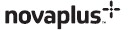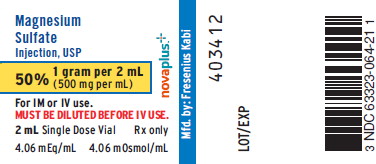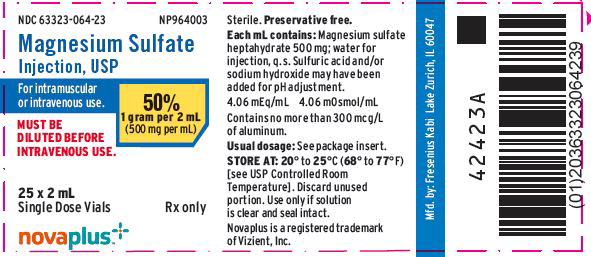 DRUG LABEL: Magnesium Sulfate
NDC: 63323-064 | Form: INJECTION, SOLUTION
Manufacturer: Fresenius Kabi USA, LLC
Category: prescription | Type: HUMAN PRESCRIPTION DRUG LABEL
Date: 20260113

ACTIVE INGREDIENTS: MAGNESIUM SULFATE HEPTAHYDRATE 500 mg/1 mL
INACTIVE INGREDIENTS: SULFURIC ACID; SODIUM HYDROXIDE

Magnesium Sulfate Injection, USP

50%

DESCRIPTION

Magnesium Sulfate Injection, USP 50% is a sterile, nonpyrogenic, concentrated solution of magnesium sulfate heptahydrate in Water for Injection. It is administered by the intravenous (IV) or intramuscular (IM) routes as an electrolyte replenisher or anticonvulsant. Must be diluted before IV use.

Each mL contains: Magnesium sulfate heptahydrate 500 mg; Water for Injection q.s. Sulfuric acid and/or sodium hydroxide may have been added for pH adjustment. The pH of a 5% solution is between 5.5 and 7.0. (Osmolarity: 4,060 mOsmol/L (calc.); 2.03 mM/mL magnesium sulfate anhydrous; 4.06 mEq/mL magnesium sulfate anhydrous).

The solution contains no bacteriostat, antimicrobial agent or added buffer (except for pH adjustment) and is intended only for use as a single dose injection. When smaller doses are required the unused portion should be discarded with the entire unit.

Magnesium sulfate heptahydrate is chemically designated MgSO4•7H2O, with a molecular weight of 246.47 and occurs as colorless crystals or white powder freely soluble in water.

CLINICAL PHARMACOLOGY

Magnesium is an important cofactor for enzymatic reactions and plays an important role in neurochemical transmission and muscular excitability.

As a nutritional adjunct in hyperalimentation, the precise mechanism of action for magnesium is uncertain. Early symptoms of hypomagnesemia (less than 1.5 mEq/L) may develop as early as three to four days or within weeks.

Predominant deficiency effects are neurological, e.g., muscle irritability, clonic twitching and tremors. Hypocalcemia and hypokalemia often follow low serum levels of magnesium. While there are large stores of magnesium present intracellularly and in the bones of adults, these stores often are not mobilized sufficiently to maintain plasma levels. Parenteral magnesium therapy repairs the plasma deficit and causes deficiency symptoms and signs to cease.

Magnesium prevents or controls convulsions by blocking neuromuscular transmission and decreasing the amount of acetylcholine liberated at the end-plate by the motor nerve impulse. Magnesium is said to have a depressant effect on the central nervous system (CNS), but it does not adversely affect the woman, fetus or neonate when used as directed in eclampsia or pre-eclampsia. Normal plasma magnesium levels range from 1.5 to 2.5 mEq/L.

As plasma magnesium rises above 4 mEq/L, the deep tendon reflexes are first decreased and then disappear as the plasma level approaches 10 mEq/L. At this level respiratory paralysis may occur. Heart block also may occur at this or lower plasma levels of magnesium. Serum magnesium concentrations in excess of 12 mEq/L may be fatal.

Magnesium acts peripherally to produce vasodilation. With low doses only flushing and sweating occur, but larger doses cause lowering of blood pressure. The central and peripheral effects of magnesium poisoning are antagonized to some extent by IV administration of calcium.

Pharmacokinetics

With IV administration the onset of anticonvulsant action is immediate and lasts about 30 minutes. Following IM administration, the onset of action occurs in about one hour and persists for three to four hours. Effective anticonvulsant serum levels range from 2.5 to 7.5 mEq/L. Magnesium is excreted solely by the kidneys at a rate proportional to the plasma concentration and glomerular filtration.

INDICATIONS AND USAGE

Magnesium Sulfate Injection, USP is suitable for replacement therapy in magnesium deficiency, especially in acute hypomagnesemia accompanied by signs of tetany similar to those observed in hypocalcemia. In such cases, the serum magnesium level is usually below the lower limit of normal (1.5 to 2.5 mEq/L) and the serum calcium level is normal (4.3 to 5.3 mEq/L) or elevated.

In total parenteral nutrition (TPN), magnesium sulfate may be added to the nutrient admixture to correct or prevent hypomagnesemia which can arise during the course of therapy.

Magnesium sulfate injection is also indicated for the prevention and control of seizures in a pre-eclampsia and eclampsia, respectively.

CONTRAINDICATIONS

Parenteral administration of the drug is contraindicated in patients with heart block or myocardial damage.

WARNINGS

FETAL HARM: Continuous administration of magnesium sulfate beyond 5 to 7 days to pregnant women can lead to hypocalcemia and bone abnormalities in the developing fetus. These bone abnormalities include skeletal demineralization and osteopenia. In addition, cases of neonatal fracture have been reported. The shortest duration of treatment that can lead to fetal harm is not known. Magnesium sulfate should be used during pregnancy only if clearly needed. If magnesium sulfate is given for treatment of preterm labor, the woman should be informed that the efficacy and safety of such use have not been established and that use of magnesium sulfate beyond 5 to 7 days may cause fetal abnormalities.

ALUMINUM TOXICITY: This product contains aluminum that may be toxic. Aluminum may reach toxic levels with prolonged parenteral administration if kidney function is impaired. Premature neonates are particularly at risk because their kidneys are immature, and they require large amounts of calcium and phosphate solutions, which contain aluminum.

Research indicates that patients with impaired kidney function, including premature neonates, who receive parenteral levels of aluminum at greater than 4 to 5 mcg/kg/day accumulate aluminum at levels associated with central nervous system and bone toxicity. Tissue loading may occur at even lower rates of administration.

Parenteral use in the presence of renal insufficiency may lead to magnesium intoxication. IV use in eclampsia should be reserved for immediate control of life-threatening convulsions.

PRECAUTIONS

General

Administer with caution if flushing and sweating occurs. When barbiturates, narcotics or other hypnotics (or systemic anesthetics) are to be given in conjunction with magnesium, their dosage should be adjusted with caution because of additive CNS depressant effects of magnesium.

Because magnesium is removed from the body solely by the kidneys, the drug should be used with caution in patients with renal impairment. Urine output should be maintained at a level of 100 mL or more during the four hours preceding each dose. Monitoring serum magnesium levels and the patient’s clinical status is essential to avoid the consequences of overdosage in toxemia. Clinical indications of a safe dosage regimen include the presence of the patellar reflex (knee jerk) and absence of respiratory depression (approximately 16 breaths or more/min). When repeated doses of the drug are given parenterally, knee jerk reflexes should be tested before each dose and if they are absent, no additional magnesium should be given until they return. Serum magnesium levels usually sufficient to control convulsions range from 3 to 6 mg/100 mL (2.5 to 5 mEq/L). The strength of the deep tendon reflexes begins to diminish when magnesium levels exceed 4 mEq/L. Reflexes may be absent at 10 mEq magnesium/L, where respiratory paralysis is a potential hazard. An injectable calcium salt should be immediately available to counteract the potential hazards of magnesium intoxication in eclampsia.

Magnesium sulfate injection (50%) must be diluted to a concentration of 20% or less prior to IV infusion. Rate of administration should be slow and cautious, to avoid producing hypermagnesemia. The 50% solution also should be diluted to 20% or less for IM injection in infants and children.

Laboratory Tests

Magnesium sulfate injection should not be given unless hypomagnesemia has been confirmed and the serum concentration of magnesium is monitored. The normal serum level is 1.5 to 2.5 mEq/L.

Drug Interactions

CNS Depressants—When barbiturates, narcotics or other hypnotics (or systemic anesthetics), or other CNS depressants are to be given in conjunction with magnesium, their dosage should be adjusted with caution because of additive CNS depressant effects of magnesium. CNS depression and peripheral transmission defects produced by magnesium may be antagonized by calcium.

Neuromuscular Blocking Agents—Excessive neuromuscular block has occurred in patients receiving parenteral magnesium sulfate and a neuromuscular blocking agent; these drugs should be administered concomitantly with caution.

Cardiac Glycosides—Magnesium sulfate should be administered with extreme caution in digitalized patients, because serious changes in cardiac conduction which can result in heart block may occur if administration of calcium is required to treat magnesium toxicity.

Pregnancy

Teratogenic Effects:

Pregnancy Category D (See WARNINGS and PRECAUTIONS)

See WARNINGS and PRECAUTIONS.

Magnesium sulfate can cause fetal abnormalities when administered beyond 5 to 7 days to pregnant women. There are retrospective epidemiological studies and case reports documenting fetal abnormalities such as hypocalcemia, skeletal demineralization, osteopenia and other skeletal abnormalities with continuous maternal administration of magnesium sulfate for more than 5 to 7 days.^1-10 Magnesium sulfate injection should be used during pregnancy only if clearly needed. If this drug is used during pregnancy, the woman should be apprised of the potential hazard to the fetus.

Nonteratogenic Effects:

When administered by continuous IV infusion (especially for more than 24 hours preceding delivery) to control convulsions in a toxemic woman, the newborn may show signs of magnesium toxicity, including neuromuscular or respiratory depression (see OVERDOSAGE).

Labor and Delivery

Continuous administration of magnesium sulfate is an unapproved treatment for preterm labor. The safety and efficacy of such use have not been established. The administration of magnesium sulfate outside of its approved indication in pregnant women should be by trained obstetrical personnel in a hospital setting with appropriate obstetrical care facilities.

Nursing Mothers

Since magnesium is distributed into milk during parenteral magnesium sulfate administration, the drug should be used with caution in nursing women.

Geriatrics

Geriatric patients often require reduced dosage because of impaired renal function. In patients with severe impairment, dosage should not exceed 20 g in 48 hours. Serum magnesium should be monitored in such patients.

ADVERSE REACTIONS

The adverse effects of parenterally administered magnesium usually are the result of magnesium intoxication. These include flushing, sweating, hypotension, depressed reflexes, flaccid paralysis, hypothermia, circulatory collapse, cardiac and CNS depression proceeding to respiratory paralysis. Hypocalcemia with signs of tetany secondary to magnesium sulfate therapy for eclampsia has been reported.

OVERDOSAGE

Magnesium intoxication is manifested by a sharp drop in blood pressure and respiratory paralysis. Disappearance of the patellar reflex is a useful clinical sign to detect the onset of magnesium intoxication. In the event of overdosage, artificial ventilation must be provided until a calcium salt can be injected IV to antagonize the effects of magnesium.

For Treatment of Overdose

Artificial respiration is often required. Intravenous calcium, 10 to 20 mL of a 5% solution (diluted if desirable with isotonic sodium chloride for injection) is used to counteract effects of hypermagnesemia. Subcutaneous physostigmine, 0.5 to 1 mg may be helpful.

Hypermagnesemia in the newborn may require resuscitation and assisted ventilation via endotracheal intubation or intermittent positive pressure ventilation as well as IV calcium.

DOSAGE AND ADMINISTRATION

Dosage of magnesium sulfate must be carefully adjusted according to individual requirements and response, and administration of the drug should be discontinued as soon as the desired effect is obtained.

Both IV and IM administration are appropriate. IM administration of the undiluted 50% solution results in therapeutic plasma levels in 60 minutes, whereas IV doses will provide a therapeutic level almost immediately. The rate of IV injection should generally not exceed 150 mg/minute (1.5 mL of a 10% concentration or its equivalent), except in severe eclampsia with seizures (see below). Continuous maternal administration of magnesium sulfate in pregnancy beyond 5 to 7 days can cause fetal abnormalities.

Solutions for IV infusion must be diluted to a concentration of 20% or less prior to administration. The diluents commonly used are 5% Dextrose Injection, USP and 0.9% Sodium Chloride Injection, USP. Deep IM injection of the undiluted (50%) solution is appropriate for adults, but the solution should be diluted to a 20% or less concentration prior to such injection in children.

In Magnesium Deficiency

In the treatment of mild magnesium deficiency, the usual adult dose is 1 g, equivalent to 8.12 mEq of magnesium (2 mL of the 50% solution) injected IM every six hours for four doses (equivalent to a total of 32.5 mEq of magnesium per 24 hours). For severe hypomagnesemia, as much as 250 mg (approximately 2 mEq) per kg of body weight (0.5 mL of the 50% solution) may be given IM within a period of four hours if necessary. Alternatively, 5 g (approximately 40 mEq) can be added to one liter of 5% Dextrose Injection, USP or 0.9% Sodium Chloride Injection, USP for slow IV infusion over a three-hour period. In the treatment of deficiency states, caution must be observed to prevent exceeding the renal excretory capacity.

In Hyperalimentation

In TPN, maintenance requirements for magnesium are not precisely known. The maintenance dose used in adults ranges from 8 to 24 mEq (1 to 3 g) daily; for infants, the range is 2 to 10 mEq (0.25 to 1.25 g) daily.

In Pre-eclampsia or Eclampsia

In severe pre-eclampsia or eclampsia, the total initial dose is 10 to 14 g of magnesium sulfate. Intravenously, a dose of 4 to 5 g in 250 mL of 5% Dextrose Injection, USP or 0.9% Sodium Chloride Injection, USP may be infused. Simultaneously, IM doses of up to 10 g (5 g or 10 mL of the undiluted 50% solution in each buttock) are given. Alternatively, the initial IV dose of 4 g may be given by diluting the 50% solution to a 10 or 20% concentration; the diluted fluid (40 mL of a 10% solution or 20 mL of a 20% solution) may then be injected IV over a period of three to four minutes. Subsequently, 4 to 5 g (8 to 10 mL of the 50% solution) are injected IM into alternate buttocks every four hours as needed, depending on the continuing presence of the patellar reflex and adequate respiratory function. Alternatively, after the initial IV dose, some clinicians administer 1 to 2 g/hour by constant IV infusion. Therapy should continue until paroxysms cease. A serum magnesium level of 6 mg/100 mL is considered optimal for control of seizures. A total daily (24 hr) dose of 30 to 40 g should not be exceeded. In the presence of severe renal insufficiency, the maximum dosage of magnesium sulfate is 20 grams/48 hours and frequent serum magnesium concentrations must be obtained. Continuous use of magnesium sulfate in pregnancy beyond 5 to 7 days can cause fetal abnormalities.

Other uses

In counteracting the muscle-stimulating effects of barium poisoning, the usual dose of magnesium sulfate is 1 to 2 g given IV.

For controlling seizures associated with epilepsy, glomerulonephritis or hypothyroidism, the usual adult dose is 1 g administered IM or IV.

In paroxysmal atrial tachycardia, magnesium should be used only if simpler measures have failed and there is no evidence of myocardial damage. The usual dose is 3 to 4 g (30 to 40 mL of a 10% solution) administered IV over 30 seconds with extreme caution.

For reduction of cerebral edema, 2.5 g (25 mL of a 10% solution) is given IV.

Incompatibilities

Magnesium sulfate in solution may result in a precipitate formation when mixed with solutions containing:

Alcohol (in high concentrations) | Heavy metals
Alkali carbonates and bicarbonates | Hydrocortisone sodium succinate
Alkali hydroxides | Phosphates
Arsenates | Polymyxin B sulfate
Barium | Procaine hydrochloride
Calcium | Salicylates
Clindamycin phosphate | Strontium
 | Tartrates

The potential incompatibility will often be influenced by the changes in the concentration of reactants and the pH of the solutions.

It has been reported that magnesium may reduce the antibiotic activity of streptomycin, tetracycline and tobramycin when given together.

Parenteral drug products should be inspected visually for particulate matter and discoloration prior to administration, whenever solution and container permit.

HOW SUPPLIED

Product Code | Unit of Sale | Each | Magnesium Sulfate Heptahydrate | Fill Volume | Magnesium mg/mL | Sulfate mg/mL
NP964003* | NDC 63323-064-23 Unit of 25 | NDC 63323-064-21 | 500 mg per mL | 2 mL | 49.3 | 194.7
*Packaged in glass vials.

Do not administer unless solution is clear and seal is intact. Contains no preservative. Discard unused portion.

Store at 20° to 25°C (68° to 77°F) [see USP Controlled Room Temperature].

REFERENCES

1. Yokoyama K, Takahashi N, Yada Y. Prolonged maternal magnesium administration and bone metabolism in neonates. Early Hum Dev. 2010;86(3):187-91. Epub 2010 Mar 12.
2. Wedig KE, Kogan J, Schorry EK et al. Skeletal demineralization and fractures caused by fetal magnesium toxicity. J Perinatol. 2006; 26(6):371-4.
3. Nassar AH, Sakhel K, Maarouf H, et al. Adverse maternal and neonatal outcome of prolonged course of magnesium sulfate tocolysis. Acta Obstet Gynecol Scan. 2006;85(9):1099-103.
4. Malaeb SN, Rassi A, Haddad MC. Bone mineralization in newborns whose mothers received magnesium sulphate for tocolysis of premature labor. Pediatr Radiol. 2004;34(5):384-6. Epub 2004 Feb 18.
5. Matsuda Y, Maeda Y, Ito M, et al. Effect of magnesium sulfate treatment on neonatal bone abnormalities. Gynecol Obstet Invest. 1997;44(2):82-8.
6. Schanler RJ, Smith LG, Burns PA. Effects of long-term maternal intravenous magnesium sulfate therapy on neonatal calcium metabolism and bone mineral content. Gynecol Obstet Invest. 1997;43(4):236-41.
7. Santi MD, Henry GW, Douglas GL. Magnesium sulfate treatment of preterm labor as a cause of abnormal neonatal bone mineralization. J Pediatr Orthop. 1994;14(2):249-53.
8. Holcomb WL, Shackelford GD, Petrie RH. Magnesium tocolysis and neonatal bone abnormalities: a controlled study. Obstet Gynecol. 1991; 78(4):611-4.
9. Cumming WA, Thomas VJ. Hypermagnesemia: a cause of abnormal metaphyses in the neonate. Am J Roentgenol. 1989; 152(5):1071-2.
10. Lamm CL, Norton KL, Murphy RJ. Congenital rickets associated with magnesium sulfate infusion for tocolysis. J Pediatr. 1988; 113(6):1078-82.
11. McGuinness GA, Weinstein MM, Cruikshank DP, et al. Effects of magnesium sulfate treatment on perinatal calcium metabolism. II. Neonatal responses. Obstet Gynecol. 1980;56(5): 595-600.
12. Riaz M, Porat R, Brodsky NL, et al. The effects of maternal magnesium sulfate treatment on newborns: a prospective controlled study. J Perinatol. 1998;18(6 pt 1):449-54.

Novaplus is a registered trademark of Vizient, Inc.

Manufactured by:

Fresenius Kabi

Lake Zurich, IL 60047
www.fresenius-kabi.com/us

451362B

Revised: January 2021

PACKAGE LABEL

PACKAGE LABEL - PRINCIPAL DISPLAY - Magnesium Sulfate 2 mL Single Dose Vial Label

Magnesium Sulfate Injection, USP

50% 1 gram per 2 mL (500 mg per mL)

For IM or IV use.

MUST BE DILUTED BEFORE IV USE.

2 mL Single Dose Vial Rx only

4.06 mEq/mL 4.06 mOsmol/mL

PACKAGE LABEL

PACKAGE LABEL - PRINCIPAL DISPLAY - Magnesium Sulfate 2 mL Single Dose Vial Tray Label
NDC 63323-064-23

NP964003

Magnesium Sulfate Injection, USP

For intramuscular or intravenous use.

50% 1 gram per 2 mL (500 mg per mL)

MUST BE DILUTED BEFORE INTRAVENOUS USE.

25 x 2 mL
Single Dose Vials

Rx only